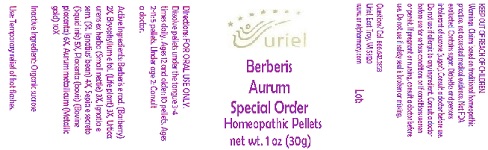 DRUG LABEL: Berberis Aurum Special Order
NDC: 48951-2036 | Form: PELLET
Manufacturer: Uriel Pharmacy Inc.
Category: homeopathic | Type: HUMAN OTC DRUG LABEL
Date: 20180601

ACTIVE INGREDIENTS: BERBERIS VULGARIS ROOT BARK 2 [hp_X]/1 1; KALANCHOE DAIGREMONTIANA LEAF 3 [hp_X]/1 1; URTICA URENS 3 [hp_X]/1 1; STRYCHNOS IGNATII SEED 4 [hp_X]/1 1; SEPIA OFFICINALIS JUICE 5 [hp_X]/1 1; BOS TAURUS PLACENTA 6 [hp_X]/1 1; GOLD 10 [hp_X]/1 1
INACTIVE INGREDIENTS: SUCROSE

Berberis Aurum Special Order

INDICATIONS AND USAGE

Directions: FOR ORAL USE ONLY.

DOSAGE AND ADMINISTRATION

Dissolve pellets under the tongue 3-4 times daily. Ages 12 and older: 10 pellets. Ages 2-11: 5 pellets. Under age 2: Consult a doctor.

ACTIVE INGREDIENT

Active Ingredients: Berberis e rad. 2X, Bryophyllum e fol. 3X, Urtica urens ex herba 3X, Ignatia e sem. 4X, Sepia e secreto 5X, Placenta (bovis) 6X, Aurum metallicum 10X

Inactive Ingredient: Organic sucrose

PURPOSE

Use: Temporary relief of hot flashes.

KEEP OUT OF REACH OF CHILDREN.

WARNINGS

Warnings: Claims based on traditional homeopathic practice, not accepted medical evidence. Not FDA evaluated. Contains sugar. Diabetics and persons intolerant of sucrose (sugar): Consult a doctor before use. Do not use if allergic to any ingredient. Consult a doctor before use for serious conditions or if conditions worsen or persist. If pregnant or nursing, consult a doctor before use. Do not use if safety seal is broken or missing.

QUESTIONS

Questions? Call 866.642.2858 Uriel, East Troy, WI 53120 www.urielpharmacy.com